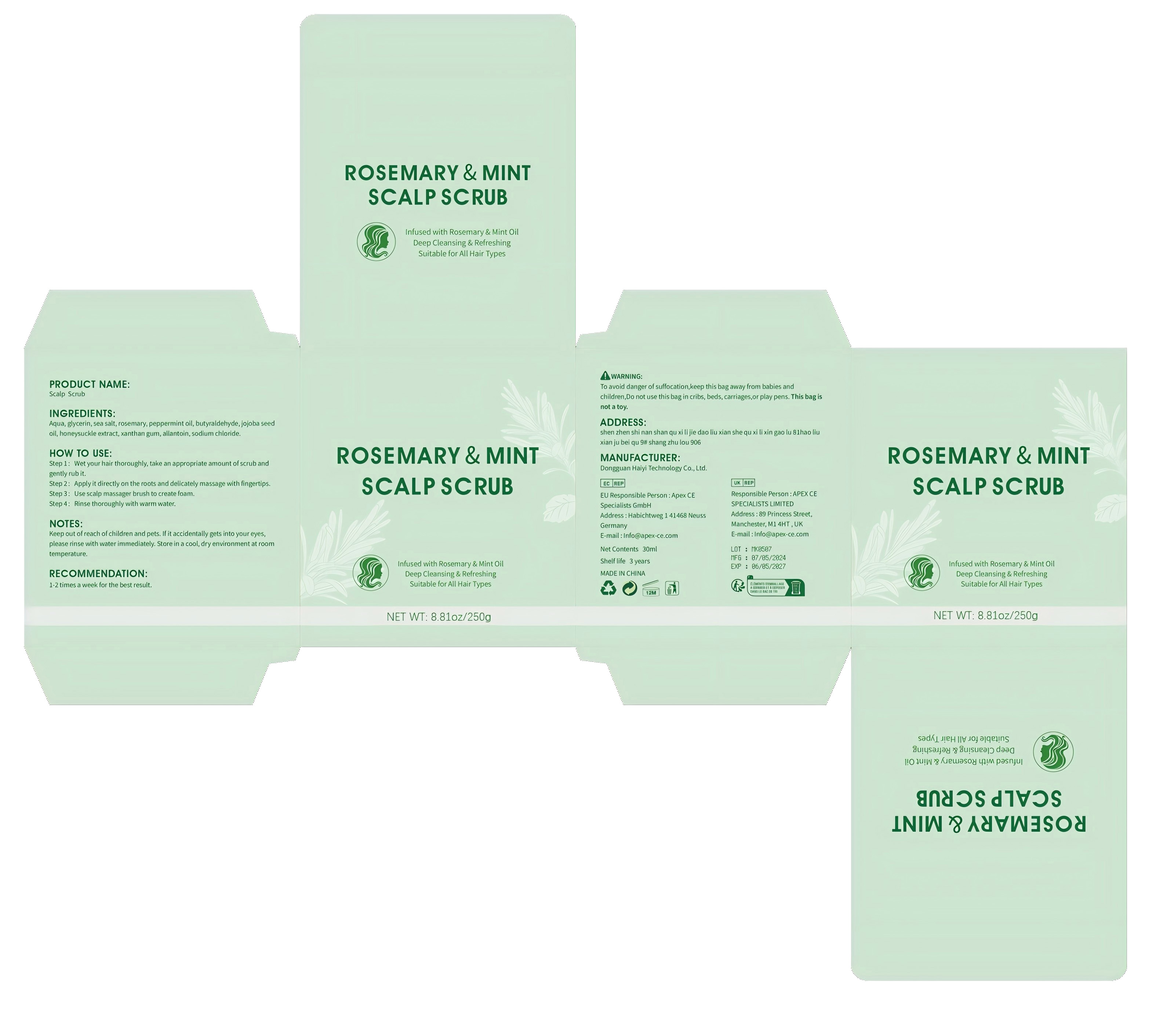 DRUG LABEL: Scalp Scrub
NDC: 84732-044 | Form: CREAM
Manufacturer: Dongguan Haiyi Technology Co.,Ltd.
Category: otc | Type: HUMAN OTC DRUG LABEL
Date: 20241014

ACTIVE INGREDIENTS: GLYCERIN 1 mg/100 g
INACTIVE INGREDIENTS: SEA SALT; SODIUM CHLORIDE; PEPPERMINT OIL; XANTHAN GUM; JOJOBA OIL; BUTYRALDEHYDE; ROSEMARY; ALLANTOIN; WATER

Active ingredient

glycerin

Inactive ingredient

Aqua, sea salt, rosemary, peppermint oil, butyraldehyde, jojoba seedoil, honeysuckle extract, xanthan gum, allantoin, sodium chloride.

Purpose section

Infused with Rosemary & Mint Oil Deep Cleansing& Refreshing Suitable for All Hair Types

Warning

1).For external use only, avoid directcontact with eyes, lf you feel any
discomfort, stop using itand wash it with plenty of water. In severe cases,
pleaseseek medical attention in time.
2). Not allowed to be used ondamaged skin,

stop use

This product may cause allergic reactions in asmall number of people.
lf youexperience any discomfort,please stop using it immediately.

not use

Not suitable for use by children, pregnantor breast feeding people.

OUT OF CHILDREN

KEEP THE PRODUCT OUT OF REACH OF CHILDREN to

HOW TO USE

Step 1: Wet your hair thoroughly, take an appropriate amount ofscrub andgently rub it.
Step 2: Applyit directly on the roots and delicately massage with fingertips.
Step 3:Use scalp massager brush to create foam.
Step 4: Rinse thoroughly with warm water.

Dosage

take an appropriateamount,Use 2-3 times a week